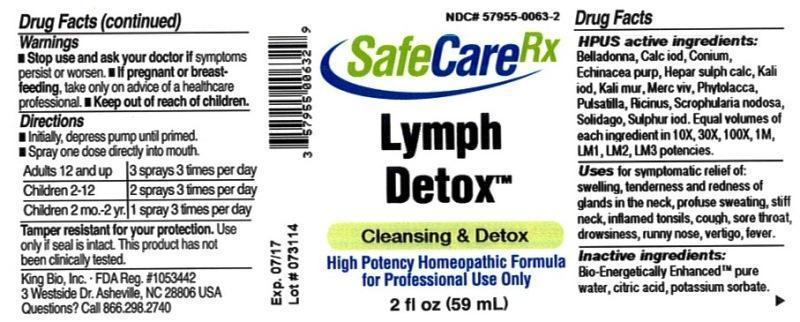 DRUG LABEL: Lymph Detox
NDC: 57955-0063 | Form: LIQUID
Manufacturer: King Bio Inc.
Category: homeopathic | Type: HUMAN OTC DRUG LABEL
Date: 20150223

ACTIVE INGREDIENTS: ATROPA BELLADONNA 10 [hp_X]/59 mL; CALCIUM IODIDE 10 [hp_X]/59 mL; CONIUM MACULATUM FLOWERING TOP 10 [hp_X]/59 mL; ECHINACEA PURPUREA 10 [hp_X]/59 mL; CALCIUM SULFIDE 10 [hp_X]/59 mL; POTASSIUM IODIDE 10 [hp_X]/59 mL; POTASSIUM CHLORIDE 10 [hp_X]/59 mL; MERCURY 10 [hp_X]/59 mL; PHYTOLACCA AMERICANA ROOT 10 [hp_X]/59 mL; PULSATILLA VULGARIS 10 [hp_X]/59 mL; RICINUS COMMUNIS SEED 10 [hp_X]/59 mL; SCROPHULARIA NODOSA 10 [hp_X]/59 mL; SOLIDAGO VIRGAUREA FLOWERING TOP 10 [hp_X]/59 mL; SULFUR IODIDE 10 [hp_X]/59 mL
INACTIVE INGREDIENTS: WATER; ANHYDROUS CITRIC ACID; POTASSIUM SORBATE

Lymph Detox™

ACTIVE INGREDIENT

Drug Facts__________________________________________________________________________________________________________

HPUS active ingredients: Belladonna, Calcarea iodata, Conium maculatum, Echinacea purpurea, Hepar sulphuris calcareum, Kali iodatum, Kali muriaticum, Mercurius vivus, Phytolacca decandra, Pulsatilla, Ricinus communis, Scrophularia nodosa, Solidago virgaurea, Sulphur iodatum. Equal volumes of each ingredient in 10X, 30X, 100X, 1M, LM1, LM2, LM3 potencies.

INDICATIONS AND USAGE

Uses for symptomatic relief of: swelling, tenderness and redness of glands in the neck, profuse sweating, stiff neck, inflamed tonsils, cough, sore throat, drowsiness, runny nose, vertigo, fever.

Inactive Ingredients:

Bio-Energetically Enhanced™ pure water, citric acid and potassium sorbate.

Warnings

- Stop use and ask your doctor if symptoms persist or worsen.
- If pregnant or breast-feeding, take only on advice of a healthcare professional.

- Keep out of reach of children.

Directions

- Initially, depress pump until primed.
- Spray one dose directly into mouth.
- Adults 12 and up: 3 sprays 3 times per day
- Children 2-12: 2 sprays 3 times per day
- Children 2 mo-2yr: 1 spray 3 times per day

OTHER SAFETY INFORMATION

Tamper resistant for your protection. Use only if safety seal is intact. This product has not been clinically tested.

PURPOSE

Uses for symptomatic relief of:

- swelling, tenderness and redness of glands in the neck
- profuse sweating
- stiff neck
- inflamed tonsils
- cough
- sore throat
- drowsiness
- runny nose
- vertigo
- fever